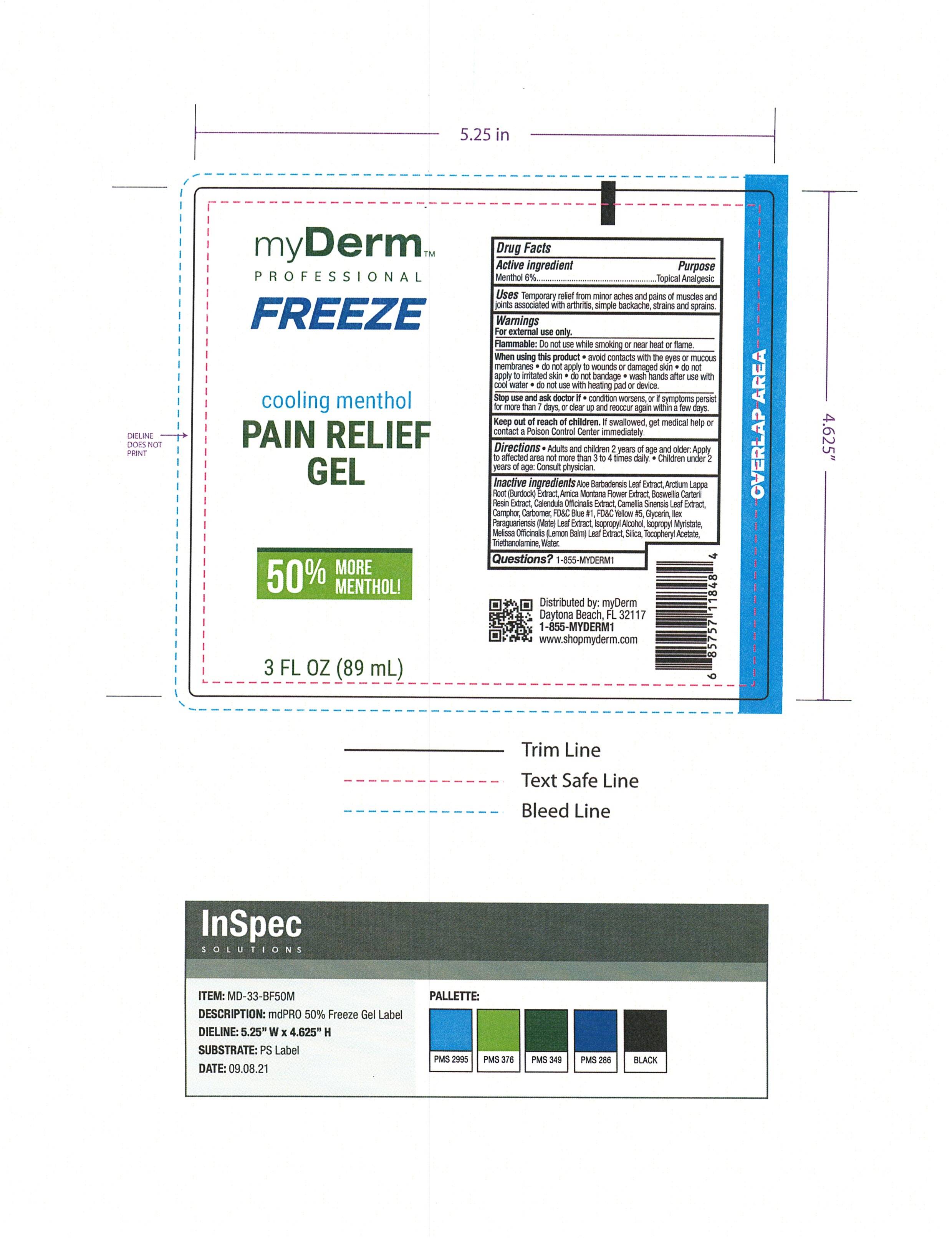 DRUG LABEL: myDerm Cooling Menthol Pain Relief  with 50 Percent More Menthol
NDC: 72667-021 | Form: GEL
Manufacturer: Inspec Solutions LLC.
Category: otc | Type: HUMAN OTC DRUG LABEL
Date: 20260216

ACTIVE INGREDIENTS: MENTHOL 6 g/100 mL
INACTIVE INGREDIENTS: ISOPROPYL MYRISTATE; CALENDULA OFFICINALIS FLOWER; FD&C YELLOW NO. 5; SILICON DIOXIDE; ARCTIUM LAPPA ROOT; CAMPHOR (NATURAL); MELISSA OFFICINALIS LEAF; .ALPHA.-TOCOPHEROL ACETATE; GREEN TEA LEAF; WATER; ILEX PARAGUARIENSIS LEAF; ISOPROPYL ALCOHOL; CARBOMER 940; ALOE VERA LEAF; TROLAMINE; ARNICA MONTANA FLOWER; FRANKINCENSE; FD&C BLUE NO. 1; GLYCERIN

myDerm Cooling Menthol Pain Relief Gel with 50% More Menthol

Active ingredient

Menthol 4%

PURPOSE

Menthol 4% ........... Topical analgesic

INDICATIONS AND USAGE

Uses Temporary relief of pain

WARNINGS

For external use only

DO not use in large quantities over raw surfaces and blistered area

When using this product

Use only as directed, read and follow all directions and warnings on this label, rare cases of serious burn have been reported with product of this type, do not bandage tightly or apply local heat (such as heating pads) to the area of use or use with medicated patch, avoid contact with eyes and mucous membranes

Stop use and ask doctor if, condition worsens, redness is present, irritation develops, symptoms persist for more than 7 days or clear up and occur again within a few days.

Keep out of reach of children, if swallowed, get medical help or contact a Poison Control Center right away.

Directions

adults and children 2 years of age and older: Apply to affected area no more than 3 to 4 times daily. Wash hands with soap. Children under 2 years of age: consult a doctor.

Inactive ingredients

Aloe Barbadensis Leaf Extract

Arctium Lappa Root (Burdock) Extract

Arnica Montana Flower Extract

Boswellia Carterii Resin Extract

Calendula Officinalis Extract

Camellia Sinensis Leaf Extract

Camphor

Carbomer FD&C Blue #1

FD&C Yellow #5

Full Spectrum Industrial Hemp Extract

Glycerin

Ilex Paraguariensis (Mate) Leaf Extract

Isopropyl Alcohol

Isopropyl Myristate

Melissa Officinalis (Lemon Balm) Leaf Extract

Silica

Tocopheryl Acetate

Triethanolamine

Water